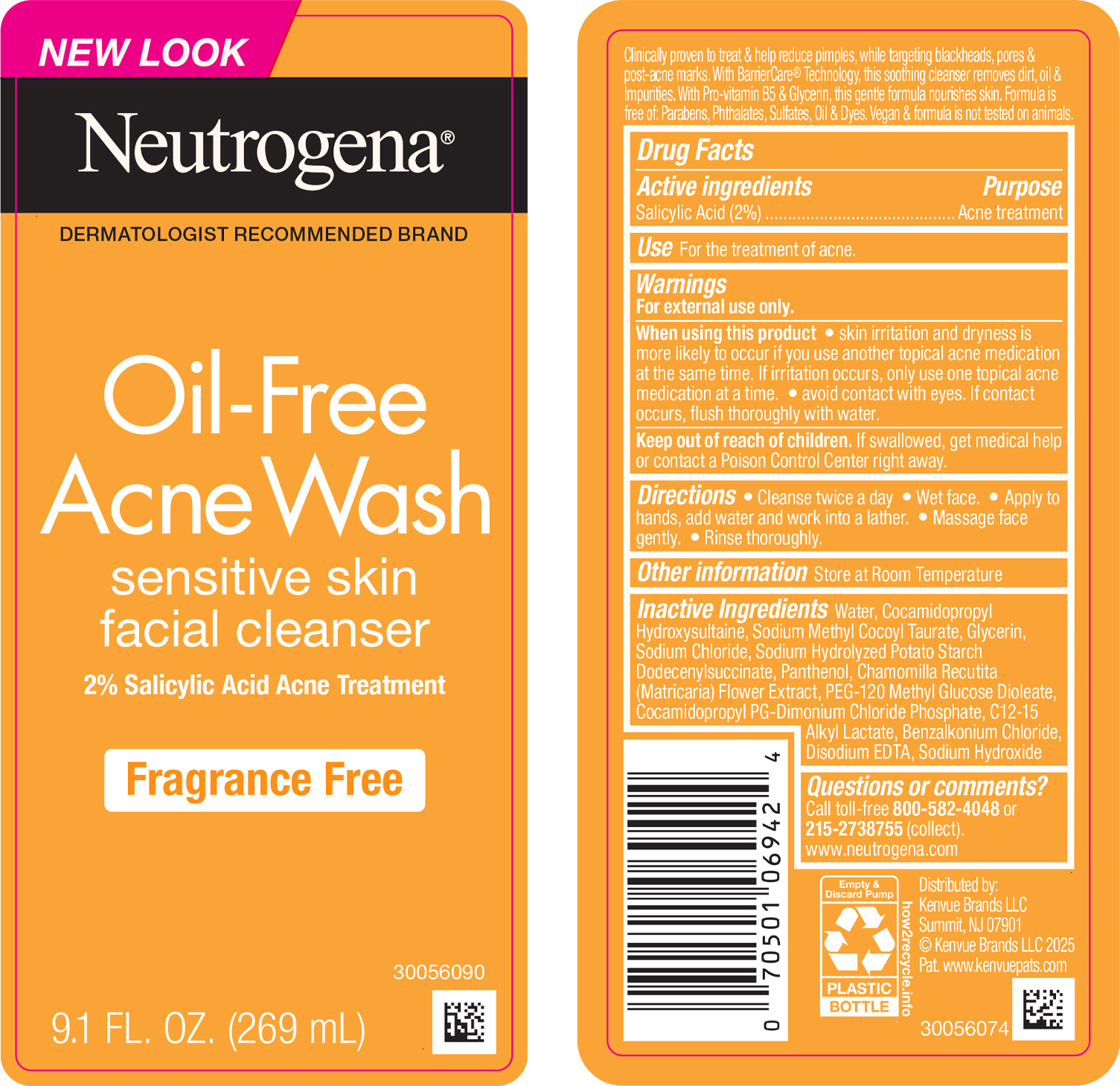 DRUG LABEL: Neutrogena Oil-Free Acne Wash Sensitive Skin Facial Cleanser Fragrance Free
NDC: 69968-0889 | Form: LIQUID
Manufacturer: Kenvue Brands LLC
Category: otc | Type: HUMAN OTC DRUG LABEL
Date: 20250318

ACTIVE INGREDIENTS: SALICYLIC ACID 20 mg/1 mL
INACTIVE INGREDIENTS: WATER; COCAMIDOPROPYL PG-DIMONIUM CHLORIDE PHOSPHATE; GLYCERIN; SODIUM HYDROLYZED POTATO STARCH DODECENYLSUCCINATE; SODIUM HYDROXIDE; COCAMIDOPROPYL HYDROXYSULTAINE; SODIUM METHYL COCOYL TAURATE; PANTHENOL; CHAMOMILE; BENZALKONIUM CHLORIDE; EDETATE DISODIUM; SODIUM CHLORIDE; PEG-120 METHYL GLUCOSE DIOLEATE; C12-15 ALKYL LACTATE

Neutrogena Oil-Free Acne Wash Sensitive Skin Facial Cleanser Fragrance Free

Drug Facts

Active ingredient

Salicylic Acid (2%)

Purpose

Acne treatment

Use

For the treatment of acne

Warnings

For external use only

▪ When using this product

▪ Skin irritation and dryness is more likely to occur if you use another topical acne medication at the same time. If irritation occurs, only use one topical acne medication at a time.

▪ Avoid contact with eyes. If contact occurs, flush thoroughly with water.

▪ Keep out of reach of children. If swallowed, get medical help or contact a Poison Control Center right away.

Directions

▪ Cleanse twice a day.

▪ Wet face. Apply to hands, add water and work into a lather.

▪ Massage face gently.

▪ Rinse thoroughly.

Other information

Store at Room Temperature

Inactive ingredients

Water, Cocamidopropyl Hydroxysultaine, Sodium Methyl Cocoyl Taurate, Glycerin, Sodium Chloride, Sodium Hydrolyzed Potato Starch Dodecenylsuccinate, Panthenol, Chamomilla Recutita (Matricaria) Flower Extract, PEG-120 Methyl Glucose Dioleate, Cocamidopropyl PG-Dimonium Chloride Phosphate, C12-15 Alkyl Lactate, Benzalkonium Chloride, Disodium EDTA, Sodium Hydroxide

Questions?

Call toll-free 800-582-4048 or 215-273-8755 (collect). www.neutrogena.com

Distributed by:
Kenvue brands LLC

Summit, NJ 07901

PRINCIPAL DISPLAY PANEL - 269 mL Bottle Label

NEW LOOK

Neutrogena®

DERMATOLOGIST RECOMMENDED BRAND

Oil-Free

Acne Wash

sensitive skin

facial cleanser

2% Salicylic Acid Acne Treatment

Fragrance Free

9.1 FL. OZ. (269mL)